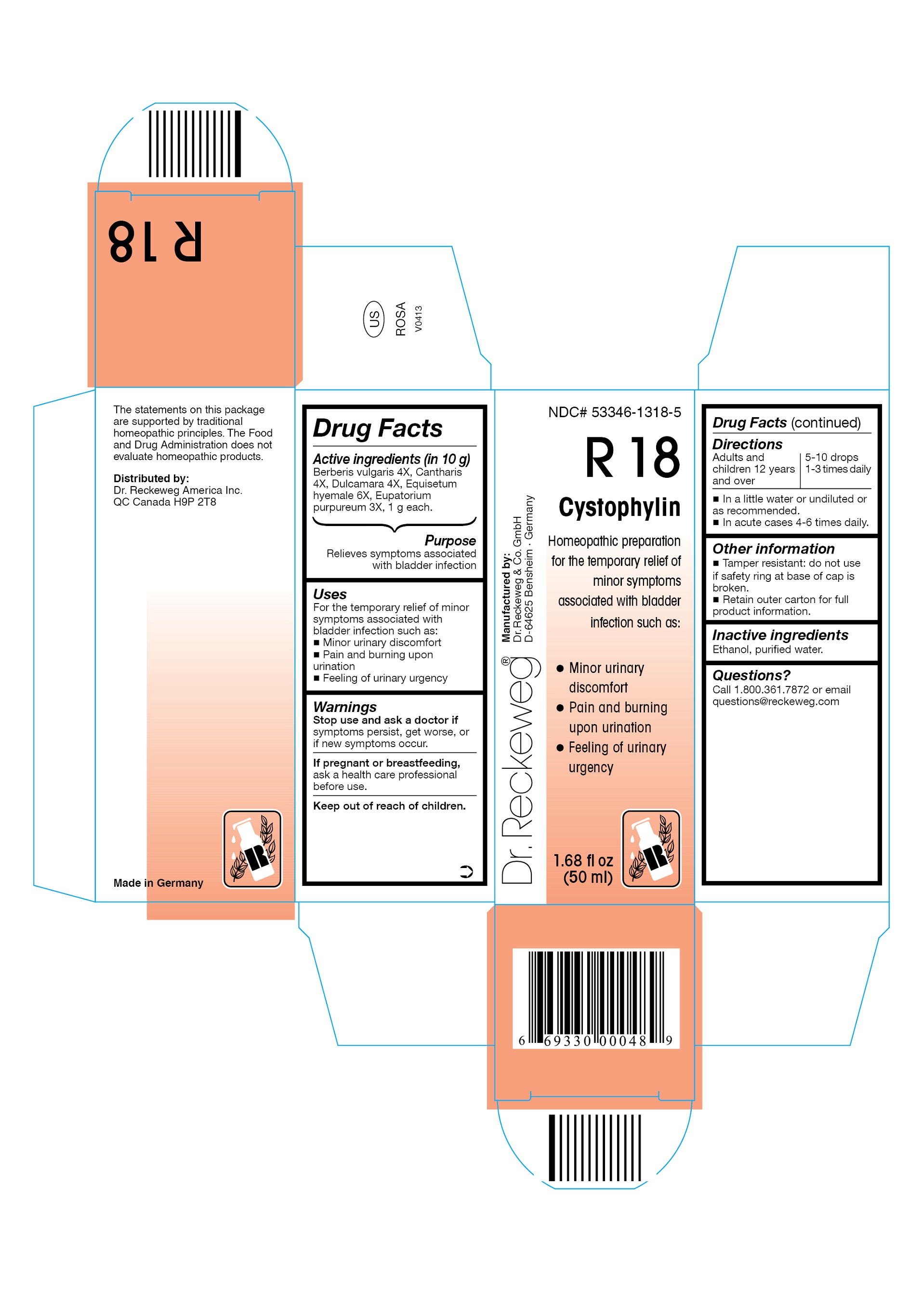 DRUG LABEL: DR. RECKEWEG R18 Cystophylin
NDC: 53346-1318 | Form: LIQUID
Manufacturer: PHARMAZEUTISCHE FABRIK DR. RECKEWEG & CO
Category: homeopathic | Type: HUMAN OTC DRUG LABEL
Date: 20130404

ACTIVE INGREDIENTS: BERBERIS VULGARIS ROOT BARK 4 [hp_X]/50 mL; LYTTA VESICATORIA 4 [hp_X]/50 mL; SOLANUM DULCAMARA TOP 4 [hp_X]/50 mL; EQUISETUM HYEMALE 6 [hp_X]/50 mL; EUTROCHIUM PURPUREUM ROOT 3 [hp_X]/50 mL
INACTIVE INGREDIENTS: ALCOHOL; WATER

DR. RECKEWEG R18 Cystophylin

Active ingredients

Berberis vulgaris 4X, Cantharis 4X, Dulcamara 4X, Equisetum hyemale 6X, Eupatorium purpureum 3X, 1 g each in 10 g.

Purpose

Relieves symptoms associated with bladder infection

Uses

For the temporary relief of minor symptoms associated with bladder infection such as:

- Minor urinary discomfort
- Pain and burning upon urination
- Feeling of urinary urgency

Warnings

Stop use and ask a doctor if symptoms persist, get worse, or if new symptoms occur.

PREGNANCY OR BREAST FEEDING

If pregnant or breastfeeding, ask a health care professional before use.

Keep out of reach of children.

Directions

Adults and children ≥ 12 years 5-10 drops 1-3 times daily, acute cases 4-6 times in a little water or undiluted or as recommended.

Other information

- Tamper resistant: do not use if safety ring at base of cap is broken.
- Retain outer carton for full product information.

Inactive ingredients

Ethanol, purified water.

Questions?

Call 1-800-361-7872 or email questions@reckeweg.com

PACKAGE LABEL

NDC# 53346-1318-5

Dr. Reckeweg R18 Cystophylin

Homeopathic preparation for the temporary relief of minor symptoms associated with bladder infection such as:

- Minor urinary discomfort
- Pain and burning upon urination
- Feeling or urinary urgency

Manufactured by:

Dr. Reckeweg Co. GmbH

D-64625 Bensheim

Germany

1.68 fl oz
(50 ml)